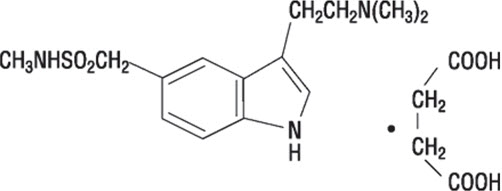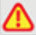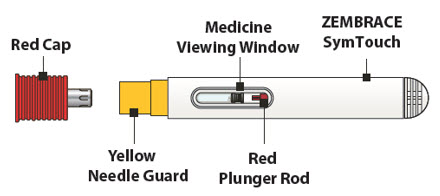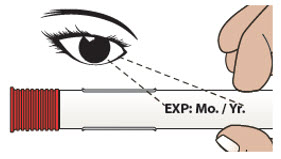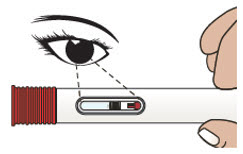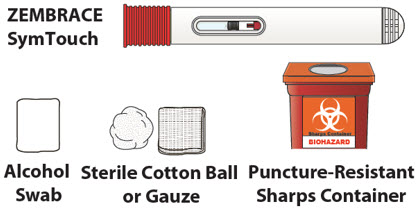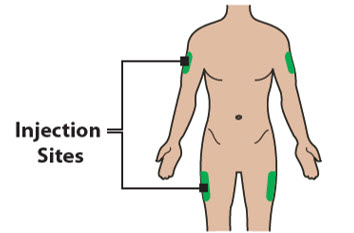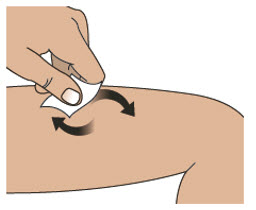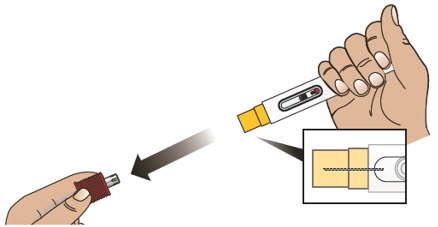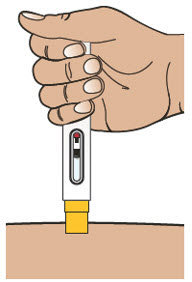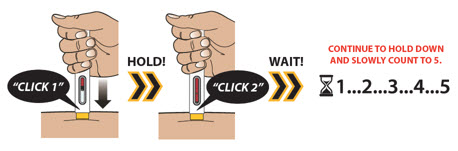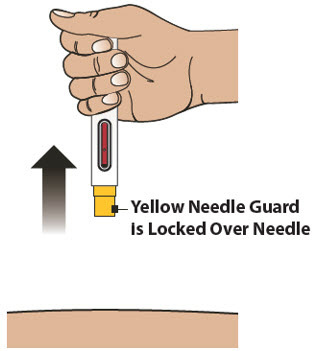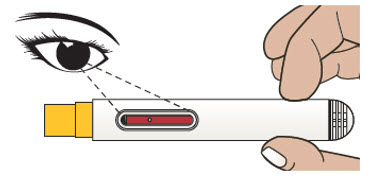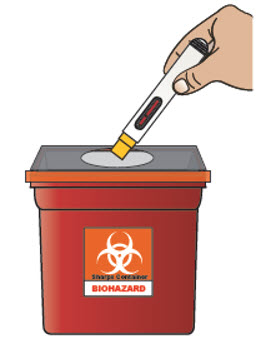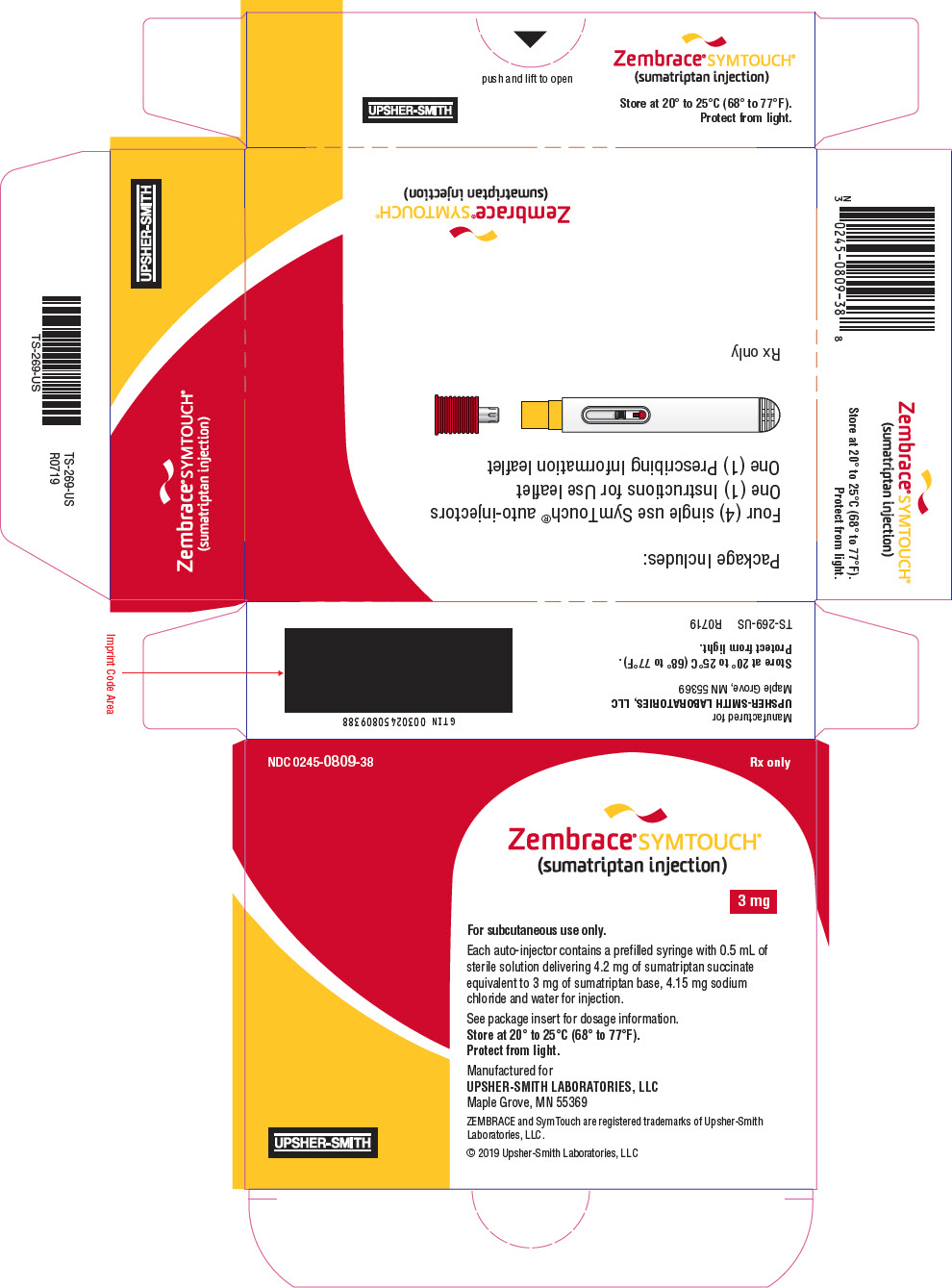 DRUG LABEL: ZEMBRACE SYMTOUCH
NDC: 0245-0809 | Form: INJECTION, SOLUTION
Manufacturer: Upsher-Smith laboratories, LLC
Category: prescription | Type: HUMAN PRESCRIPTION DRUG LABEL
Date: 20260109

ACTIVE INGREDIENTS: SUMATRIPTAN SUCCINATE 3 mg/1 1
INACTIVE INGREDIENTS: SODIUM CHLORIDE; WATER

HIGHLIGHTS OF PRESCRIBING INFORMATION

These highlights do not include all the information needed to use ZEMBRACE®SymTouch®safely and effectively. See full prescribing information for ZEMBRACE®SymTouch®.
ZEMBRACE®SymTouch®(sumatriptan succinate) Injection, for subcutaneous use
Initial U.S. Approval: 1992

1 INDICATIONS AND USAGE

ZEMBRACE SymTouch is a serotonin (5-HT1B/1D) receptor agonist (triptan) indicated for:

- Acute treatment of migraine with or without aura in adults. (1)

Limitations of Use:

- Use only if a clear diagnosis of migraine has been established. (1)
- Not indicated for the prophylactic therapy of migraine. (1)

2 DOSAGE AND ADMINISTRATION

- For subcutaneous use only. (2.1)
- Acute treatment of migraine: 3 mg Single dose. (2.1)
- Maximum dose in a 24-hour period: 12 mg. Separate doses by at least 1 hour. (2.1)

3 DOSAGE FORMS AND STRENGTHS

- Injection: 3 mg prefilled, ready-to-use, single-dose disposable auto-injector. (3)

4 CONTRAINDICATIONS

- History of coronary artery disease or coronary vasospasm (4)
- Wolff-Parkinson-White syndrome or other cardiac accessory conduction pathway disorders (4)
- History of stroke, transient ischemic attack, or hemiplegic or basilar migraine (4)
- Peripheral vascular disease (4)
- Ischemic bowel disease (4)
- Uncontrolled hypertension (4)
- Recent (within 24 hours) use of another 5-HT1agonist (e.g., another triptan) or of an ergotamine-containing medication (4)
- Concurrent or recent (past 2 weeks) use of monoamine oxidase-A inhibitor (4)
- Hypersensitivity to sumatriptan (angioedema and anaphylaxis seen) (4)
- Severe hepatic impairment (4)

5 WARNINGS AND PRECAUTIONS

- Myocardial ischemia/infarction and Prinzmetal's angina: Perform cardiac evaluation in patients with multiple cardiovascular risk factors. (5.1)
- Arrhythmias: Discontinue ZEMBRACE SymTouch if occurs. (5.2)
- Chest/throat/neck/jaw pain, tightness, pressure, or heaviness: Generally, not associated with myocardial ischemia; evaluate for coronary artery disease in patients at high risk. (5.3)
- Cerebral hemorrhage, subarachnoid hemorrhage, and stroke: Discontinue ZEMBRACE SymTouch if occurs. (5.4)
- Gastrointestinal ischemia and reactions, peripheral vasospastic reactions: Discontinue ZEMBRACE SymTouch if occurs. (5.5)
- Medication overuse headache: Detoxification may be necessary. (5.6)
- Serotonin syndrome: Discontinue ZEMBRACE SymTouch if occurs. (5.7)
- Seizures: Use with caution in patients with epilepsy or a lowered seizure threshold. (5.10)

6 ADVERSE REACTIONS

Most common adverse reactions (≥5% and > placebo) were injection site reactions, tingling, dizziness/vertigo, warm/hot sensation, burning sensation, feeling of heaviness, pressure sensation, flushing, feeling of tightness, and numbness/paresthesia. (6.1)

To report SUSPECTED ADVERSE REACTIONS, contact Upsher-Smith Laboratories, LLC at 1-855-899-9180 or FDA at 1-800-FDA-1088 or www.fda.gov/medwatch.

8 USE IN SPECIFIC POPULATIONS

- Pregnancy: Based on animal data, may cause fetal harm. (8.1)

FULL PRESCRIBING INFORMATION

1 INDICATIONS AND USAGE

ZEMBRACE SymTouch is indicated for the acute treatment of migraine with or without aura in adults.

Limitations of Use:

- Use only if a clear diagnosis of migraine has been established. If a patient has no response to the first migraine attack treated with ZEMBRACE SymTouch, reconsider the diagnosis before ZEMBRACE SymTouch is administered to treat any subsequent attacks.
- ZEMBRACE SymTouch injection is not indicated for the prevention of migraine attacks.

2 DOSAGE AND ADMINISTRATION

2.1 Dosing Information

The recommended dose of ZEMBRACE SymTouch is 3 mg injected subcutaneously.

The maximum cumulative injected dose that may be given in 24 hours is 12 mg, with doses of ZEMBRACE SymTouch separated by at least 1 hour. ZEMBRACE SymTouch may also be given at least 1 hour following a dose of another sumatriptan product.

2.2 Administration Using ZEMBRACE SymTouch

ZEMBRACE SymTouch is available as a prefilled, ready-to-use, single dose, disposable auto-injector containing 3 mg sumatriptan. With ZEMBRACE SymTouch, the needle penetrates approximately ¼ inch (6 mm). The injection is intended to be given subcutaneously. Do not administer by any other route. Instruct patients on the proper use of ZEMBRACE SymTouch and direct them to use injection sites with an adequate skin and subcutaneous thickness to accommodate the length of the needle.

3 DOSAGE FORMS AND STRENGTHS

Injection: 3 mg sumatriptan in 0.5 mL prefilled, ready-to-use, single dose, disposable auto-injector.

4 CONTRAINDICATIONS

ZEMBRACE SymTouch injection is contraindicated in patients with:

- Ischemic coronary artery disease (CAD) (angina pectoris, history of myocardial infarction, or documented silent ischemia) or coronary artery vasospasm, including Prinzmetal's angina [see Warnings and Precautions (5.1)] .
- Wolff-Parkinson-White syndrome or arrhythmias associated with other cardiac accessory conduction pathway disorders [see Warnings and Precautions (5.2)] .
- History of stroke or transient ischemic attack (TIA) or history of hemiplegic or basilar migraine because these patients are at a higher risk of stroke [see Warnings and Precautions (5.4)] .
- Peripheral vascular disease [see Warnings and Precautions (5.5)] .
- Ischemic bowel disease [see Warnings and Precautions (5.5)] .
- Uncontrolled hypertension [see Warnings and Precautions (5.8)] .
- Recent (i.e., within 24 hours) use of ergotamine-containing medication, ergot-type medication (such as dihydroergotamine or methysergide), or another 5-hydroxytryptamine1 (5-HT1) agonist [see Drug Interactions (7.1, 7.3)] .
- Concurrent administration of an MAO-A inhibitor or recent (within 2 weeks) use of an MAO-A inhibitor [see Drug Interactions (7.2)and Clinical Pharmacology (12.3)] .
- Known hypersensitivity to sumatriptan (angioedema and anaphylaxis seen) [see Warnings and Precautions (5.9)] .
- Severe hepatic impairment [see Clinical Pharmacology (12.3)] .

5 WARNINGS AND PRECAUTIONS

5.1 Myocardial Ischemia, Myocardial Infarction, and Prinzmetal's Angina

The use of ZEMBRACE SymTouch injection is contraindicated in patients with ischemic or vasospastic CAD. There have been rare reports of serious cardiac adverse reactions, including acute myocardial infarction, occurring within a few hours following administration of sumatriptan injection. Some of these reactions occurred in patients without known CAD. 5-HT1agonists, including ZEMBRACE SymTouch injection, may cause coronary artery vasospasm (Prinzmetal's angina), even in patients without a history of CAD.

Perform a cardiovascular evaluation in triptan-naive patients who have multiple cardiovascular risk factors (e.g., increased age, diabetes, hypertension, smoking, obesity, strong family history of CAD) prior to receiving ZEMBRACE SymTouch injection. If there is evidence of CAD or coronary artery vasospasm, ZEMBRACE SymTouch injection is contraindicated. For patients with multiple cardiovascular risk factors who have a negative cardiovascular evaluation, consider administering the first dose of ZEMBRACE SymTouch injection in a medically supervised setting and performing an electrocardiogram (ECG) immediately following ZEMBRACE SymTouch injection. For such patients, consider periodic cardiovascular evaluation in intermittent long-term users of ZEMBRACE SymTouch injection.

5.2 Arrhythmias

Life-threatening disturbances of cardiac rhythm, including ventricular tachycardia and ventricular fibrillation leading to death, have been reported within a few hours following the administration of 5-HT1agonists.

Discontinue ZEMBRACE SymTouch injection if these disturbances occur. ZEMBRACE SymTouch injection is contraindicated in patients with Wolff-Parkinson-White syndrome or arrhythmias associated with other cardiac accessory conduction pathway disorders.

5.3 Chest, Throat, Neck, and/or Jaw Pain/Tightness/Pressure

Sensations of tightness, pain, pressure, and heaviness in the precordium, throat, neck, and jaw commonly occur after treatment with sumatriptan injection and are usually non-cardiac in origin. However, perform a cardiac evaluation if these patients are at high cardiac risk. The use of ZEMBRACE SymTouch injection is contraindicated in patients with CAD and those with Prinzmetal's variant angina.

5.4 Cerebrovascular Events

Cerebral hemorrhage, subarachnoid hemorrhage, and stroke have occurred in patients treated with 5-HT1agonists, and some have resulted in fatalities. In a number of cases, it appears possible that the cerebrovascular events were primary, the 5-HT1agonist having been administered in the incorrect belief that the symptoms experienced were a consequence of migraine when they were not. Also, patients with migraine may be at increased risk of certain cerebrovascular events (e.g., stroke, hemorrhage, TIA). Discontinue ZEMBRACE SymTouch injection if a cerebrovascular event occurs.

Before treating headaches in patients not previously diagnosed with migraine or in patients who present with atypical symptoms, exclude other potentially serious neurological conditions. ZEMBRACE SymTouch injection is contraindicated in patients with a history of stroke or TIA.

5.5 Other Vasospasm Reactions

ZEMBRACE SymTouch injection may cause non-coronary vasospastic reactions, such as peripheral vascular ischemia, gastrointestinal vascular ischemia and infarction (presenting with abdominal pain and bloody diarrhea), splenic infarction, and Raynaud's syndrome. In patients who experience symptoms or signs suggestive of non-coronary vasospasm reaction following the use of any 5-HT1agonist, rule out a vasospastic reaction before receiving additional ZEMBRACE SymTouch injections.

Reports of transient and permanent blindness and significant partial vision loss have been reported with the use of 5-HT1agonists. Since visual disorders may be part of a migraine attack, a causal relationship between these events and the use of 5-HT1agonists have not been clearly established.

5.6 Medication Overuse Headache

Overuse of acute migraine drugs (e.g., ergotamine, triptans, opioids, combination of these drugs for 10 or more days per month) may lead to exacerbation of headache (medication overuse headache). Medication overuse headache may present as migraine-like daily headaches, or as a marked increase in frequency of migraine attacks. Detoxification of patients, including withdrawal of the overused drugs, and treatment of withdrawal symptoms (which often includes a transient worsening of headache) may be necessary.

5.7 Serotonin Syndrome

Serotonin syndrome may occur with ZEMBRACE SymTouch injection, particularly during co-administration with selective serotonin reuptake inhibitors (SSRIs), serotonin norepinephrine reuptake inhibitors (SNRIs), tricyclic antidepressants (TCAs), and MAO inhibitors [see Drug Interactions (7.4)] . Serotonin syndrome symptoms may include mental status changes (e.g., agitation, hallucinations, coma), autonomic instability (e.g., tachycardia, labile blood pressure, hyperthermia), neuromuscular aberrations (e.g., hyperreflexia, incoordination), and/or gastrointestinal symptoms (e.g., nausea, vomiting, diarrhea). The onset of symptoms usually occurs within minutes to hours of receiving a new or a greater dose of a serotonergic medication. Discontinue ZEMBRACE SymTouch injection if serotonin syndrome is suspected.

5.8 Increase in Blood Pressure

Significant elevation in blood pressure, including hypertensive crisis with acute impairment of organ systems, has been reported on rare occasions in patients treated with 5-HT1agonists, including patients without a history of hypertension. Monitor blood pressure in patients treated with ZEMBRACE SymTouch. ZEMBRACE SymTouch injection is contraindicated in patients with uncontrolled hypertension.

5.9 Hypersensitivity Reactions

Hypersensitivity reactions, including angioedema and anaphylaxis, have occurred in patients receiving sumatriptan. Such reactions can be life-threatening or fatal. In general, anaphylactic reactions to drugs are more likely to occur in individuals with a history of sensitivity to multiple allergens. ZEMBRACE SymTouch injection is contraindicated in patients with a history of hypersensitivity reaction to sumatriptan.

5.10 Seizures

Seizures have been reported following administration of sumatriptan. Some have occurred in patients with either a history of seizures or concurrent conditions predisposing to seizures. There are also reports in patients where no such predisposing factors are apparent. ZEMBRACE SymTouch injection should be used with caution in patients with a history of epilepsy or conditions associated with a lowered seizure threshold.

6 ADVERSE REACTIONS

The following serious adverse reactions are described below and elsewhere in the labeling:

- Myocardial ischemia, myocardial infarction, and Prinzmetal's angina [see Warnings and Precautions (5.1)]
- Arrhythmias [see Warnings and Precautions (5.2)]
- Chest, throat, neck, and/or jaw pain/tightness/pressure [see Warnings and Precautions (5.3)]
- Cerebrovascular events [see Warnings and Precautions (5.4)]
- Other vasospasm reactions [see Warnings and Precautions (5.5)]
- Medication overuse headache [see Warnings and Precautions (5.6)]
- Serotonin syndrome [see Warnings and Precautions (5.7)]
- Increase in blood pressure [see Warnings and Precautions (5.8)]
- Hypersensitivity reactions [see Contraindications (4), Warnings and Precautions (5.9)]
- Seizures [see Warnings and Precautions (5.10)]

6.1 Clinical Trials Experience

Because clinical trials are conducted under widely varying conditions, adverse reaction rates observed in the clinical trials of a drug cannot be directly compared with rates in the clinical trials of another drug and may not reflect the rates observed in practice.

Adverse Reactions in Placebo-Controlled Trials with Sumatriptan Injection

Migraine Headache:Table 1 lists adverse reactions that occurred in 2 US placebo-controlled clinical trials in migraine subjects (Studies 2 and 3), following either a single 6-mg dose of sumatriptan injection or placebo. Only reactions that occurred at a frequency of 2% or more in groups treated with sumatriptan injection 6 mg and that occurred at a frequency greater than the placebo group are included in Table 1.

Table 1: Adverse Reactions in Pooled Placebo-Controlled Trials in Patients with Migraine (Studies 2 and 3)
Adverse Reaction | Percent of Subjects Reporting
Adverse Reaction | Sumatriptan Injection 6 mg Subcutaneous (n = 547) | Placebo (n = 370)
Atypical sensations | 42 | 9
Tingling | 14 | 3
Warm/hot sensation | 11 | 4
Burning sensation | 7 | <1
Feeling of heaviness | 7 | 1
Pressure sensation | 7 | 2
Feeling of tightness | 5 | <1
Numbness | 5 | 2
Feeling strange | 2 | <1
Tight feeling in head | 2 | <1
Cardiovascular
Flushing | 7 | 2
Chest discomfort | 5 | 1
Tightness in chest | 3 | <1
Pressure in chest | 2 | <1
Ear, nose, and throat
Throat discomfort | 3 | <1
Discomfort: nasal cavity/sinuses | 2 | <1
Injection site reaction [Includes injection site pain, stinging/burning, swelling, erythema, bruising, bleeding.] | 59 | 24
Miscellaneous
Jaw discomfort | 2 | 0
Musculoskeletal
Weakness | 5 | <1
Neck pain/stiffness | 5 | <1
Myalgia | 2 | <1
Neurological
Dizziness/vertigo | 12 | 4
Drowsiness/sedation | 3 | 2
Headache | 2 | <1
Skin
Sweating | 2 | 1

The incidence of adverse reactions in controlled clinical trials was not affected by gender or age of the patients. There were insufficient data to assess the impact of race on the incidence of adverse reactions.

Adverse Reactions in a Study with ZEMBRACE SymTouch

The most common adverse reactions in a placebo-controlled trial with ZEMBRACE SymTouch were injection site reactions (including injection site bruising, erythema, hemorrhage, induration, irritation, pain, paresthesia, pruritis, swelling, and urticaria), occurring in 30% of ZEMBRACE SymTouch-treated patients compared to 13% of placebo-treated patients. Adverse reactions with ZEMRACE SymTouch are expected to be similar to those observed with sumatriptan injection.

6.2 Post-marketing Experience

The following adverse reactions have been identified during post-approval use of sumatriptan tablets, sumatriptan nasal spray, and sumatriptan injection. Because these reactions are reported voluntarily from a population of uncertain size, it is not always possible to reliably estimate their frequency or establish a causal relationship to drug exposure.

Cardiovascular

Hypotension, palpitations

Neurological

Dystonia, tremor

7 DRUG INTERACTIONS

7.1 Ergot-Containing Drugs

Ergot-containing drugs have been reported to cause prolonged vasospastic reactions. Because these effects may be additive, use of ergotamine-containing or ergot-type medications (like dihydroergotamine or methysergide) and ZEMBRACE SymTouch within 24 hours of each other is contraindicated.

7.2 Monoamine Oxidase-A Inhibitors

MAO-A inhibitors increase systemic exposure by 2-fold. Therefore, the use of ZEMBRACE SymTouch injection in patients receiving MAO-A inhibitors is contraindicated [see Clinical Pharmacology (12.3)] .

7.3 Other 5-HT1Agonists

Because their vasospastic effects may be additive, coadministration of ZEMBRACE SymTouch injection and other 5-HT1agonists (e.g., triptans) within 24 hours of each other is contraindicated.

7.4 Selective Serotonin Reuptake Inhibitors/Serotonin Norepinephrine Reuptake Inhibitors and Serotonin Syndrome

Cases of serotonin syndrome have been reported during coadministration of triptans and SSRIs, SNRIs, TCAs, and MAO inhibitors [see Warnings and Precautions (5.7)] .

8 USE IN SPECIFIC POPULATIONS

8.1 Pregnancy

Risk Summary

Data from a prospective pregnancy exposure registry and epidemiological studies of pregnant women have not detected an increased frequency of birth defects or a consistent pattern of birth defects among women exposed to sumatriptan compared with the general population (see Data) . In developmental toxicity studies in rats and rabbits, oral administration of sumatriptan to pregnant animals was associated with embryo lethality, fetal abnormalities, and pup mortality. When administered by the intravenous route to pregnant rabbits, sumatriptan was embryo lethal (see Data) .

In the U.S. general population, the estimated background risk of major birth defects and of miscarriage in clinically recognized pregnancies is 2% to 4% and 15% to 20%, respectively. The reported rate of major birth defects among deliveries to women with migraine ranged from 2.2% to 2.9% and the reported rate of miscarriage was 17%, which were similar to rates reported in women without migraine.

Clinical Considerations

Disease-Associated Maternal and/or Embryo/Fetal Risk:Several studies have suggested that women with migraine may be at increased risk of preeclampsia during pregnancy.

Data

Human Data

The Sumatriptan/Naratriptan/Treximet (sumatriptan and naproxen sodium) Pregnancy Registry, a population-based international prospective study, collected data for sumatriptan from January 1996 to September 2012. The Registry documented outcomes of 626 infants and fetuses exposed to sumatriptan during pregnancy (528 with earliest exposure during the first trimester, 78 during the second trimester, 16 during the third trimester, and 4 unknown). The occurrence of major birth defects (excluding fetal deaths and induced abortions without reported defects and all spontaneous pregnancy losses) during first-trimester exposure to sumatriptan was 4.2% (20/478 [95% CI: 2.6% to 6.5%]) and during any trimester of exposure was 4.2% (24/576 [95% CI: 2.7% to 6.2%]). The sample size in this study had 80% power to detect at least a 1.73 to 1.91-fold increase in the rate of major malformations. The number of exposed pregnancy outcomes accumulated during the registry was insufficient to support definitive conclusions about overall malformation risk or for making comparisons of the frequencies of specific birth defects. Of the 20 infants with reported birth defects after exposure to sumatriptan in the first trimester, 4 infants had ventricular septal defects, including one infant who was exposed to both sumatriptan and naratriptan and 3 infants had pyloric stenosis. No other birth defect was reported for more than 2 infants in this group.

In a study using data from the Swedish Medical Birth Register, live births to women who reported using triptans or ergots during pregnancy were compared with those of women who did not. Of the 2,257 births with first-trimester exposure to sumatriptan, 107 infants were born with malformations (relative risk 0.99 [95% CI: 0.91 to 1.21]). A study using linked data from the Medical Birth Registry of Norway to the Norwegian Prescription Database compared pregnancy outcomes in women who redeemed prescriptions for triptans during pregnancy, as well as a migraine disease comparison group who redeemed prescriptions for sumatriptan before pregnancy only, compared with a population control group. Of the 415 women who redeemed prescriptions for sumatriptan during the first trimester, 15 had infants with major congenital malformations (OR 1.16 [95% CI: 0.69 to 1.94]) while for the 364 women who redeemed prescriptions for sumatriptan before, but not during, pregnancy, 20 had infants with major congenital malformations (OR 1.83 [95% CI: 1.17 to 2.88]), each compared with the population comparison group. Additional smaller observational studies evaluating use of sumatriptan during pregnancy have not suggested an increased risk of teratogenicity.

Animal Data

Oral administration of sumatriptan to pregnant rats during the period of organogenesis resulted in an increased incidence of fetal blood vessel (cervicothoracic and umbilical) abnormalities. The highest no-effect dose for embryofetal developmental toxicity in rats was 60 mg/kg/day. Oral administration of sumatriptan to pregnant rabbits during the period of organogenesis resulted in increased incidences of embryo lethality and fetal cervicothoracic vascular and skeletal abnormalities. Intravenous administration of sumatriptan to pregnant rabbits during the period of organogenesis resulted in an increased incidence of embryo lethality. The highest oral and intravenous no-effect doses for developmental toxicity in rabbits were 15 and 0.75 mg/kg/day, respectively.

Oral administration of sumatriptan to rats prior to and throughout gestation resulted in embryofetal toxicity (decreased body weight, decreased ossification, increased incidence of skeletal abnormalities). The highest no-effect dose was 50 mg/kg/day. In offspring of pregnant rats treated orally with sumatriptan during organogenesis, there was a decrease in pup survival. The highest no-effect dose for this effect was 60 mg/kg/day. Oral treatment of pregnant rats with sumatriptan during the latter part of gestation and throughout lactation resulted in a decrease in pup survival. The highest no-effect dose for this finding was 100 mg/kg/day.

8.2 Lactation

Risk Summary

Sumatriptan is excreted in human milk following subcutaneous administration (see Data) . There are no data on the effects of sumatriptan on the breastfed infant or the effects of sumatriptan on milk production.

The developmental and health benefits of breastfeeding should be considered along with the mother's clinical need for ZEMBRACE SymTouch and any potential adverse effects on the breastfed infant from sumatriptan or from the underlying maternal condition.

Clinical Considerations

Infant exposure to sumatriptan can be minimized by avoiding breastfeeding for 12 hours after treatment with ZEMBRACE SymTouch.

Data

Following subcutaneous administration of a 6 mg dose of sumatriptan injection in 5 lactating volunteers, sumatriptan was present in milk.

8.4 Pediatric Use

Safety and effectiveness in pediatric patients have not been established. ZEMBRACE SymTouch injection is not recommended for use in patients younger than 18 years of age.

Two controlled clinical trials evaluated sumatriptan nasal spray (5 to 20 mg) in 1,248 pediatric migraineurs 12 to 17 years of age who treated a single attack. The trials did not establish the efficacy of sumatriptan nasal spray compared with placebo in the treatment of migraine in pediatric patients. Adverse reactions observed in these clinical trials were similar in nature to those reported in clinical trials in adults.

Five controlled clinical trials (2 single-attack trials, 3 multiple-attack trials) evaluating oral sumatriptan (25 to 100 mg) in pediatric subjects 12 to 17 years of age enrolled a total of 701 pediatric migraineurs. These trials did not establish the efficacy of oral sumatriptan compared with placebo in the treatment of migraine in pediatric patients. Adverse reactions observed in these clinical trials were similar in nature to those reported in clinical trials in adults. The frequency of all adverse reactions in these patients appeared to be both dose- and age-dependent, with younger patients reporting reactions more commonly than older pediatric patients.

Post-marketing experience documents that serious adverse reactions have occurred in the pediatric population after use of subcutaneous, oral, and/or intranasal sumatriptan. These reports include reactions similar in nature to those reported rarely in adults, including stroke, visual loss, and death. A myocardial infarction has been reported in a 14-year-old male following the use of oral sumatriptan; clinical signs occurred within 1 day of drug administration. Clinical data to determine the frequency of serious adverse reactions in pediatric patients who might receive subcutaneous, oral, or intranasal sumatriptan are not presently available.

8.5 Geriatric Use

Clinical trials of sumatriptan injection did not include sufficient numbers of subjects aged 65 and over to determine whether they respond differently from younger patients. Other reported clinical experience has not identified differences in responses between the elderly and younger subjects. In general, dose selection for an elderly patient should be cautious, usually starting at the low end of the dosing range, reflecting the greater frequency of decreased hepatic, renal, or cardiac function and of concomitant disease or other drug therapy.

A cardiovascular evaluation is recommended for geriatric patients who have other cardiovascular risk factors (e.g., diabetes, hypertension, smoking, obesity, strong family history of CAD) prior to receiving ZEMBRACE SymTouch injection [see Warnings and Precautions (5.1)] .

10 OVERDOSAGE

Coronary vasospasm was observed after intravenous administration of sumatriptan injection [see Contraindications (4)] . Overdoses would be expected from animal data (dogs at 0.1 g/kg, rats at 2 g/kg) to possibly cause convulsions, tremor, inactivity, erythema of the extremities, reduced respiratory rate, cyanosis, ataxia, mydriasis, injection site reactions (desquamation, hair loss, and scab formation), and paralysis.

The elimination half-life of sumatriptan is about 2 hours [see Clinical Pharmacology (12.3)] , and therefore monitoring of patients after overdose with ZEMBRACE SymTouch injection should continue for at least 10 hours or while symptoms or signs persist.

It is unknown what effect hemodialysis or peritoneal dialysis has on the serum concentrations of sumatriptan.

11 DESCRIPTION

ZEMBRACE SymTouch injection contains sumatriptan succinate, a selective 5-HT1B/1Dreceptor agonist. Sumatriptan succinate is chemically designated as 3-[2-(dimethylamino) ethyl]-N-methyl-indole-5-methanesulfonamide succinate (1:1), and it has the following structure:

The empirical formula is C14H21N3O2S∙C4H6O4, representing a molecular weight of 413.5. Sumatriptan succinate is a white to off-white powder that is readily soluble in water and in saline.

ZEMBRACE SymTouch is a clear, colorless to pale yellow, sterile, nonpyrogenic solution for subcutaneous injection. Each 0.5 mL of ZEMBRACE SymTouch contains 4.2 mg of sumatriptan succinate equivalent to 3 mg of sumatriptan (base) and 4.15 mg of sodium chloride, USP in Water for Injection, USP.

The pH range of solution is approximately 4.2 to 5.3 and the osmolality of injection is approximately 291 mOsmol (275 to 315 mOsmol).

12 CLINICAL PHARMACOLOGY

12.1 Mechanism of Action

Sumatriptan binds with high affinity to human cloned 5-HT1B/1Dreceptors. Sumatriptan presumably exerts its therapeutic effects in the treatment of migraine headache through agonist effects at the 5-HT1B/1Dreceptors on intracranial blood vessels and sensory nerves of the trigeminal system, which result in cranial vessel constriction and inhibition of pro-inflammatory neuropeptide release.

12.2 Pharmacodynamics

Blood Pressure: Significant elevation in blood pressure, including hypertensive crisis, has been reported in patients with and without a history of hypertension [see Warnings and Precautions (5.8)] .

Peripheral (Small) Arteries: In healthy volunteers (N = 18), a trial evaluating the effects of sumatriptan on peripheral (small vessel) arterial reactivity failed to detect a clinically significant increase in peripheral resistance.

Heart Rate: Transient increases in blood pressure observed in some subjects in clinical trials carried out during sumatriptan's development as a treatment for migraine were not accompanied by any clinically significant changes in heart rate.

12.3 Pharmacokinetics

After a single 3 mg dose, ZEMBRACE SymTouch was bioequivalent to IMITREX subcutaneous injection.

Absorption and Bioavailability: The bioavailability of sumatriptan via subcutaneous site injection to 18 healthy male subjects was 97% ± 16% of that obtained following intravenous injection.

After a single 6-mg subcutaneous manual injection into the deltoid area of the arm in 18 healthy males (age: 24 ± 6 years, weight: 70 kg), the maximum serum concentration (Cmax) of sumatriptan was (mean ± standard deviation) 74 ± 15 ng/mL and the time to peak concentration (Tmax) was 12 minutes after injection (range: 5 to 20 minutes) .In this trial, the same dose injected subcutaneously in the thigh gave a Cmaxof 61 ± 15 ng/mL by manual injection versus 52 ±15 ng/mL by auto-injector techniques. The Tmaxor amount absorbed was not significantly altered by either the site or technique of injection.

Distribution: Protein binding, determined by equilibrium dialysis over the concentration range of 10 to 1,000 ng/mL, is low, approximately 14% to 21%. The effect of sumatriptan on the protein binding of other drugs has not been evaluated.

Following a 6-mg subcutaneous injection into the deltoid area of the arm in 9 males (mean age: 33 years, mean weight: 77 kg) the volume of distribution central compartment of sumatriptan was 50 ± 8 liters and the distribution half-life was 15 ± 2 minutes .

Metabolism: In vitrostudies with human microsomes suggest that sumatriptan is metabolized by MAO, predominantly the A isoenzyme. Most of a radiolabeled dose of sumatriptan excreted in the urine is the major metabolite indole acetic acid (IAA) or the IAA glucuronide, both of which are inactive.

Elimination: After a single 6-mg subcutaneous dose, 22% ± 4% was excreted in the urine as unchanged sumatriptan and 38% ± 7% as the IAA metabolite.

Following a 6-mg subcutaneous injection into the deltoid area of the arm, the systemic clearance of sumatriptan was 1,194 ± 149 mL/min and the terminal half-life was 115 ± 19 minutes.

Specific Populations:

Age:The pharmacokinetics of sumatriptan in the elderly (mean age: 72 years, 2 males and 4 females) and in subjects with migraine (mean age: 38 years, 25 males and 155 females) were similar to that in healthy male subjects (mean age: 30 years).

Patients with Hepatic Impairment:The effect of mild to moderate hepatic disease on the pharmacokinetics of subcutaneously administered sumatriptan has been evaluated. There were no significant differences in the pharmacokinetics of subcutaneously administered sumatriptan in moderately hepatically impaired subjects compared with healthy controls. The pharmacokinetics of subcutaneously administered sumatriptan in patients with severe hepatic impairment has not been studied. The use of ZEMBRACE SymTouch injection in this population is contraindicated [see Contraindications (4)] .

Race:The systemic clearance and Cmaxof subcutaneous sumatriptan were similar in black (n = 34) and Caucasian (n = 38) healthy male subjects.

Drug Interaction Studies:

Monoamine Oxidase-A Inhibitors:In a trial of 14 healthy females, pretreatment with an MAO-A inhibitor decreased the clearance of sumatriptan, resulting in a 2-fold increase in the area under the sumatriptan plasma concentration-time curve (AUC), corresponding to a 40% increase in elimination half-life.

13 NONCLINICAL TOXICOLOGY

13.1 Carcinogenesis, Mutagenesis, Impairment of Fertility

Carcinogenesis

In carcinogenicity studies in mouse and rat, sumatriptan was administered orally for 78 weeks and 104 weeks, respectively, at doses up to 160 mg/kg/day (the high dose in rat was reduced from 360 mg/kg/day during Week 21). The highest dose tested in mice and rats was approximately 130 and 260 times, respectively, the single MRHD of 6 mg administered subcutaneously on a mg/m^2basis. There was no evidence in either species of an increase in tumors related to sumatriptan administration.

Mutagenesis

Sumatriptan was negative in in vitro(bacterial reverse mutation [Ames], gene cell mutation in Chinese hamster V79/HGPRT, chromosomal aberration in human lymphocytes) and in vivo(rat micronucleus) assays.

Impairment of Fertility

When sumatriptan (0, 5, 50, or 500 mg/kg/day) was administered orally to male and female rats prior to and throughout the mating period, there was a treatment-related decrease in fertility secondary to a decrease in mating in animals treated with doses greater than 5 mg/kg/day. It is not clear whether this finding was due to an effect on males or females or both.

When sumatriptan was administered by subcutaneous injection to male and female rats prior to and throughout the mating period, there was no evidence of impaired fertility at doses up to 60 mg/kg/day.

13.2 Animal Toxicology and/or Pharmacology

Corneal Opacities: Dogs receiving oral sumatriptan developed corneal opacities and defects in the corneal epithelium. Corneal opacities were seen at the lowest dose tested, 2 mg/kg/day, and were present after 1 month of treatment. Defects in the corneal epithelium were noted in a 60-week study. Earlier examinations for these toxicities were not conducted and no-effect doses were not established; however, the relative plasma exposure at the lowest dose tested was approximately 3 times the human exposure after a 6-mg subcutaneous dose.

14 CLINICAL STUDIES

Clinical Studies with Sumatriptan Injection

In controlled clinical trials enrolling more than 1,000 patients during migraine attacks who were experiencing moderate or severe pain and 1 or more of the symptoms enumerated in Table 3, onset of relief began as early as 10 minutes following a 6-mg sumatriptan injection. Lower doses of sumatriptan injection may also prove effective, although the proportion of patients obtaining adequate relief was decreased and the latency to that relief is greater with lower doses.

In Study 1, 6 different doses of sumatriptan injection (n = 30 each group) were compared with placebo (n = 62), in a single-attack, parallel-group design, the dose response relationship was found to be as shown in Table 2.

Table 2: Proportion of Patients with Migraine Relief and Incidence of Adverse Reactions by Time and by Sumatriptan Dose in Study 1
Dose of Sumatriptan Injection | Percent Patients With Relief [Relief is defined as the reduction of moderate or severe pain to no or mild pain after dosing without use of rescue medication] |  |  |  | Adverse Reactions Incidence (%)
Dose of Sumatriptan Injection | at 10 Minutes | at 30 Minutes | at 1 Hour | at 2 Hours | Adverse Reactions Incidence (%)
Placebo | 5 | 15 | 24 | 21 | 55
1 mg | 10 | 40 | 43 | 40 | 63
2 mg | 7 | 23 | 57 | 43 | 63
3 mg | 17 | 47 | 57 | 60 | 77
4 mg | 13 | 37 | 50 | 57 | 80
6 mg | 10 | 63 | 73 | 70 | 83
8 mg | 23 | 57 | 80 | 83 | 93

In 2 randomized, placebo-controlled clinical trials of sumatriptan injection 6 mg in 1,104 patients with moderate or severe migraine pain (Studies 2 and 3), the onset of relief was less than 10 minutes. Headache relief, as defined by a reduction in pain from severe or moderately severe to mild or no headache, was achieved in 70% of the patients within 1 hour of a single 6-mg subcutaneous dose of sumatriptan injection. Approximately 82% and 65% of patients treated with sumatriptan 6 mg had headache relief and were pain free within 2 hours, respectively.

Table 3 shows the 1- and 2-hour efficacy results for sumatriptan injection 6 mg in Studies 2 and 3.

Table 3: Proportion of Patients with Pain Relief and Relief of Migraine Symptoms After 1 and 2 Hours of Treatment in Studies 2 and 3
1-Hour Data | Study 2 |  | Study 3
1-Hour Data | Placebo (n = 190) | Sumatriptan 6 mg (n = 384) | Placebo (n = 180) | Sumatriptan 6 mg (n = 350)
Subjects with pain relief (grade 0/1) | 18% | 70% [P<0.05 versus placebo.] | 26% | 70%
Subjects with no pain | 5% | 48% | 13% | 49%
Subjects without nausea | 48% | 73% | 50% | 73%
Subjects without photophobia | 23% | 56% | 25% | 58%
Subjects with little or no clinical disability [A successful outcome in terms of clinical disability was defined prospectively as ability to work mildly impaired or ability to work and function normally.] | 34% | 76% | 34% | 76%
2-Hour Data | Study 2 |  | Study 3
2-Hour Data | Placebo [Includes patients that may have received an additional placebo injection 1 hour after the initial injection.] | Sumatriptan 6 mg [Includes patients that may have received an additional 6 mg of sumatriptan injection 1 hour after the initial injection.] | Placebo | Sumatriptan 6 mg
Subjects with pain relief (grade 0/1) | 31% | 81% | 39% | 82%
Subjects with no pain | 11% | 63% | 19% | 65%
Subjects without nausea | 56% | 82% | 63% | 81%
Subjects without photophobia | 31% | 72% | 35% | 71%
Subjects with little or no clinical disability | 42% | 85% | 49% | 84%

Sumatriptan injection also relieved photophobia, phonophobia (sound sensitivity), nausea, and vomiting associated with migraine attacks.

The efficacy of sumatriptan injections was unaffected by whether or not the migraine was associated with aura, duration of attack, gender or age of the subject, or concomitant use of common migraine prophylactic drugs (e.g., beta-blockers).

Clinical Study with ZEMBRACE SymTouch

In a double-blind, randomized, placebo-controlled clinical trial of ZEMBRACE SymTouch, 230 patients with migraine with or without aura received either ZEMBRACE SymTouch (N=111) or placebo (N=119) for a single migraine attack. The patients had a mean age of 41 years (range 18 to 65 years); approximately 76% were White and 85% were female.

The study excluded patients with medication overuse headache, treatment with onabotulinumtoxin A within 180 days, and patients with a history of cluster headache.

The primary efficacy endpoint was the proportion of patients who were pain-free (defined as a reduction from pre-dose moderate [Grade 2] or severe [Grade 3] pain to none [Grade 0]) 2 hours after the first dose. Of the ZEMBRACE SymTouch-treated patients, 46% were pain free at 2 hours after treatment compared to 27% of the placebo-treated patients.

16 HOW SUPPLIED/STORAGE AND HANDLING

16.1 How Supplied

- ZEMBRACE®SymTouch®3 mg/0.5 mL Injection contains sumatriptan as the succinate salt and is supplied as a clear, colorless to pale yellow, sterile, nonpyrogenic solution in a prefilled, ready-to-use, single dose, disposable auto-injector unit (NDC # 0245-0809-89).
- Each carton contains 4 units (NDC # 0245-0809-38) and a Patient Information and Instructions for Use leaflet.

16.2 Storage and Handling

Store at 20° to 25°C (68° to 77°F); excursions permitted to 15° to 30°C (59° to 86°F). Protect from light.

17 PATIENT COUNSELING INFORMATION

Advise the patient to read the FDA-approved patient labeling (Patient Information and Instructions for Use).

Risk of Myocardial Ischemia and/or Infarction, Prinzmetal's Angina, Other Vasospasm-Related Events, Arrhythmias, and Cerebrovascular Events

Inform patients that ZEMBRACE SymTouch injection may cause serious cardiovascular side effects such as myocardial infarction or stroke. Although serious cardiovascular events can occur without warning symptoms, patients should be alert for the signs and symptoms of chest pain, shortness of breath, irregular heartbeat, significant rise in blood pressure, weakness, and slurring of speech and should ask for medical advice when observing any indicative sign or symptoms are observed. Apprise patients of the importance of this follow-up [see Warnings and Precautions (5.1, 5.2, 5.4, 5.5, 5.8)] .

Hypersensitivity Reactions

Inform patients that anaphylactic reactions have occurred in patients receiving sumatriptan injection. Such reactions can be life-threatening or fatal. In general, anaphylactic reactions to drugs are more likely to occur in individuals with a history of sensitivity to multiple allergens [see Contraindications (4)and Warnings and Precautions (5.9)] .

Concomitant Use with Other Triptans or Ergot Medications

Inform patients that use of ZEMBRACE SymTouch injection within 24 hours of another triptan or an ergot-type medication (including dihydroergotamine or methylsergide) is contraindicated [see Contraindications (4), Drug Interactions (7.1, 7.3)] .

Serotonin Syndrome

Caution patients about the risk of serotonin syndrome with the use of ZEMBRACE SymTouch injection or other triptans, particularly during combined use with SSRIs, SNRIs, TCAs, and MAO inhibitors [see Warnings and Precautions (5.7), Drug Interactions (7.4)] .

Medication Overuse Headache

Inform patients that use of acute migraine drugs for 10 or more days per month may lead to an exacerbation of headache and encourage patients to record headache frequency and drug use (e.g., by keeping a headache diary) [see Warnings and Precautions (5.6)] .

Pregnancy

Advise patients to notify their healthcare provider if they become pregnant during treatment or plan to become pregnant [see Use in Specific Populations (8.1)] .

Lactation

Advise patients to notify their healthcare provider if they are breastfeeding or plan to breastfeed [see Use in Specific Populations (8.2)] .

Ability to Perform Complex Tasks

Treatment with ZEMBRACE SymTouch injection may cause somnolence and dizziness; instruct patients to evaluate their ability to perform complex tasks during migraine attacks and after administration of ZEMBRACE SymTouch injection.

How to Use ZEMBRACE SymTouch

Provide patients instruction on the proper use of ZEMBRACE SymTouch injection if they are able to self-administer ZEMBRACE SymTouch injection in medically unsupervised conditions.

Inform patients that the needle in the ZEMBRACE SymTouch penetrates approximately ¼ of an inch (6 mm). Inform patients that the injection is intended to be given subcutaneously and intramuscular or intravascular delivery should be avoided. Instruct patients to use injection sites with an adequate skin and subcutaneous thickness to accommodate the length of the needle.

Manufactured for
UPSHER-SMITH LABORATORIES, LLC
Maple Grove, MN 55369

ZEMBRACE and SymTouch are registered trademarks of Upsher-Smith Laboratories, LLC.

This product may be covered by one or more U.S. patent(s). See www.uslpatents.com.

Revised: 2/2021

Patient Information
ZEMBRACE®SymTouch® (Zem-brace Sim-Touch)
(sumatriptan succinate)
Injection

What is the most important information I should know about ZEMBRACE SymTouch?

ZEMBRACE SymTouch can cause serious side effects, including:
Heart attack and other heart problems. Heart problems may lead to death.

Stop taking ZEMBRACE SymTouch and get emergency medical help right away if you have any of the following symptoms of a heart attack:

- discomfort in the center of your chest that lasts for more than a few minutes, or that goes away and comes back
- severe tightness, pain, pressure, or heaviness in your chest, throat, neck, or jaw
- pain or discomfort in your arms, back, neck, jaw, or stomach
- shortness of breath with or without chest discomfort
- breaking out in a cold sweat
- nausea or vomiting
- feeling lightheaded

ZEMBRACE SymTouch is not for people with risk factors for heart disease unless a heart exam is done and shows no problem. You have a higher risk for heart disease if you:

- have high blood pressure
- have high cholesterol levels
- smoke
- are overweight
- have diabetes
- have a family history of heart disease

What is ZEMBRACE SymTouch?

ZEMBRACE SymTouch is a prescription medicine used to treat acute migraine headaches with or without aura in adults who have been diagnosed with migraine.

ZEMBRACE SymTouch is not used to treat other types of headaches such as hemiplegic (that make you unable to move on one side of your body) or basilar (rare form of migraine with aura) migraines.

ZEMBRACE SymTouch is not used to prevent or decrease the number of migraines you have.

It is not known if ZEMBRACE SymTouch is safe and effective in children under 18 years of age.

Who should not take ZEMBRACE SymTouch?

Do not take ZEMBRACE SymTouch if you have:

- heart problems or a history of heart problems
- narrowing of blood vessels to your legs, arms, stomach, or kidney (peripheral vascular disease)
- uncontrolled high blood pressure
- hemiplegic migraines or basilar migraines. If you are not sure if you have these types of migraines, ask your healthcare provider.
- had a stroke, transient ischemic attacks (TIAs), or problems with your blood circulation
- severe liver problems
- an allergy to sumatriptan or any of the ingredients in ZEMBRACE SymTouch. See the end of this leaflet for a complete list of ingredients in ZEMBRACE SymTouch.
- taken any of the following medicines in the last 24 hours:
  - almotriptan
  - eletriptan
  - frovatriptan
  - naratriptan
  - rizatriptan
  - ergotamines
  - dihydroergotamine

Ask your healthcare provider if you are not sure if your medicine is listed above.

What should I tell my healthcare provider before taking ZEMBRACE SymTouch?

Before taking ZEMBRACE SymTouch, tell your healthcare provider about all of your medical conditions, including if you:

- have high blood pressure
- have high cholesterol
- have diabetes
- smoke
- are overweight
- have heart problems or family history of heart problems or stroke
- have kidney problems
- have liver problems
- have had epilepsy or seizures
- are not using effective birth control
- are pregnant or plan to become pregnant. It is not known if ZEMBRACE SymTouch can harm your unborn baby.
- are breastfeeding or plan to breastfeed. ZEMBRACE SymTouch passes into your breast milk. It is not known if this can harm your baby. Talk with your healthcare provider about the best way to feed your baby if you take ZEMBRACE SymTouch.

Tell your healthcare provider about all the medicines you take,including prescription and over-the-counter medicines, vitamins, and herbal supplements. Using ZEMBRACE SymTouch with certain other medicines can affect each other, causing serious side effects.

Especially tell your healthcare provider ifyou take anti-depressant medicines called:

- selective serotonin reuptake inhibitors (SSRIs)
- serotonin norepinephrine reuptake inhibitors (SNRIs)
- tricyclic antidepressants (TCAs)
- monoamine oxidase inhibitors (MAOIs)

Ask your healthcare provider or pharmacist for a list of these medicines if you are not sure.

Know the medicines you take. Keep a list of them to show your healthcare provider or pharmacist when you get a new medicine.

How should I take ZEMBRACE SymTouch?

- Certain people should take their first dose of ZEMBRACE SymTouch in their healthcare provider's office or in another medical setting. Ask your healthcare provider if you should take your first dose in a medical setting.
- Use ZEMBRACE SymTouch exactly as your healthcare provider tells you to use it.
- Your healthcare provider may change your dose. Do not change your dose without first talking with your healthcare provider.
- For adults, the usual dose is a single injection given just below the skin.
- You should give an injection as soon as the symptoms of your headache start, but it may be given at any time during a migraine headache attack.
- If you did not get any relief after the first injection, do not give a second injection without first talking with your healthcare provider.
- You may use a second dose of ZEMBRACE SymTouch after the first dose of ZEMBRACE SymTouch OR after one dose of another sumatriptan medication separated by at least 1 hour, but not sooner, if your headache comes back or you only get some relief after your first injection.
- Do not take more than a total of 12 mg of ZEMBRACE SymTouch in a 24-hour period. Talk to your doctor about how many ZEMBRACE SymTouch you can take in a 24-hour period if you take another form of sumatriptan medication in between ZEMBRACE SymTouch.
- If you use too much ZEMBRACE SymTouch, call your healthcare provider or go to the nearest hospital emergency room right away.
- You should write down when you have headaches and when you take ZEMBRACE SymTouch so you can talk with your healthcare provider about how ZEMBRACE SymTouch is working for you.

What should I avoid while taking ZEMBRACE SymTouch?

ZEMBRACE SymTouch can cause dizziness, weakness, or drowsiness. If you have these symptoms, do not drive a car, use machinery, or do anything where you need to be alert.

What are the possible side effects of ZEMBRACE SymTouch?

See " What is the most important information I should know about ZEMBRACE SymTouch?"

ZEMBRACE SymTouch may cause serious side effects, including:

- changes in color or sensation in your fingers and toes (Raynaud's syndrome)
- stomach and intestinal problems(gastrointestinal and colonic ischemic events). Symptoms of gastrointestinal and colonic ischemic events include:
  - sudden or severe stomach pain
  - stomach pain after meals
  - weight loss
  - nausea or vomiting
  - constipation or diarrhea
  - bloody diarrhea
  - fever
- problems with blood circulation to your legs and feet (peripheral vascular ischemia).Symptoms of peripheral vascular ischemia include:
  - cramping and pain in your legs or hips
  - feeling of heaviness or tightness in your leg muscles
  - burning or aching pain in your feet or toes while resting
  - numbness, tingling, or weakness in your legs
  - cold feeling or color changes in 1 or both legs or feet
- hives (itchy bumps); swelling of your tongue, mouth, or throat.
- medication overuse headaches.Some people who use too many ZEMBRACE SymTouch injections may have worse headaches (medication overuse headache). If your headaches get worse, your healthcare provider may decide to stop your treatment with ZEMBRACE SymTouch.
- serotonin syndrome. Serotonin syndrome is a rare but serious problem that can happen in people using ZEMBRACE SymTouch, especially if ZEMBRACE SymTouch is used with anti-depressant medicines called SSRIs or SNRIs. Call your healthcare provider right away if you have any of the following symptoms of serotonin syndrome:
  - mental changes such as seeing things that are not there (hallucinations), agitation, or coma
  - fast heartbeat
  - changes in blood pressure
  - high body temperature
  - tight muscles
  - trouble walking
- seizures. Seizures have happened in people taking ZEMBRACE SymTouch who have never had seizures before. Talk with your healthcare provider about your chance of having seizures while you take ZEMBRACE SymTouch.

The most common side effects of ZEMBRACE SymTouch include:

- pain or redness at your injection site
- tingling or numbness in your fingers or toes
- dizziness
- warm, hot, burning feeling to your face (flushing)
- discomfort or stiffness in your neck
- feeling weak, drowsy, or tired

Tell your healthcare provider if you have any side effect that bothers you or that does not go away.

These are not all the possible side effects of ZEMBRACE SymTouch. Call your doctor for medical advice about side effects. You may report side effects to FDA at 1-800-FDA-1088.

How should I store ZEMBRACE SymTouch?

- Store between 68° to 77°F (20° to 25°C)
- Store your medicine away from light.
- Keep your medicine in the packaging or carrying case provided with it.

Keep ZEMBRACE SymTouch and all medicines out of the reach of children.

General information about the safe and effective use of ZEMBRACE SymTouch.

Medicines are sometimes prescribed for purposes other than those listed in Patient Information leaflets. Do not use ZEMBRACE SymTouch for a condition for which it was not prescribed. Do not give ZEMBRACE SymTouch to other people, even if they have the same symptoms you have. It may harm them.

This Patient Information leaflet summarizes the most important information about ZEMBRACE SymTouch. If you would like more information, talk with your healthcare provider. You can ask your healthcare provider or pharmacist for information about ZEMBRACE SymTouch that is written for healthcare professionals.

For more information, go to www.upsher-smith.com or call 1-888-650-3789.

What are the ingredients in ZEMBRACE SymTouch Injection?

Active ingredient: sumatriptan succinate
Inactive ingredients: sodium chloride, water for injection

Manufactured for
UPSHER-SMITH LABORATORIES, LLC
Maple Grove, MN 55369

ZEMBRACE and SymTouch are registered trademarks of Upsher-Smith Laboratories, LLC.

This product may be covered by one or more U.S. patent(s). See www.uslpatents.com.

This Patient Information has been approved by the U.S. Food and Drug Administration.

Revised: 2/2021

Instructions for Use
ZEMBRACE®SymTouch® (Zem-brace Sim-Touch)
(sumatriptan succinate)
Injection

Read this Instructions for Use before you start to use the ZEMBRACE®SymTouch®. There may be new information. This information does not take the place of talking with your healthcare provider about your medical condition or treatment. You and your healthcare provider should talk about ZEMBRACE SymTouch when you start taking it and at regular checkups.
The ZEMBRACE SymTouch Auto-injector is a single-use, pre-filled injection device with the exact dose you need. The device should be used only 1 time and then discarded.

Important Precautions
Keep out of reach of children.
Do notuse after the expiration date has passed.
Do notstore or expose to high temperatures.
Do notfreeze.
Do notremove the Red Cap until you are ready to inject.
Do notuse if dropped after removing the Red Cap.
Do notput or press thumb, fingers or hand over the Yellow Needle Guard.

Step 1 – Inspect Auto-injector and Gather Supplies

1A – Remove Auto-injector from the carton

1B – Check the Expiration Date on the Auto-injector

Do notuse if the expiration date has passed.

1C – Inspect the medicine through the Medicine Viewing Window
Inspect the appearance of ZEMBRACE SymTouch Auto-injector medicine through the medicine window. It must be a clear, colorless to pale yellow solution.

Do notinject the medicine if the solution looks discolored or cloudy or contains lumps, flakes, or particles.

1D – Gather the following supplies

1. Auto-injector
2. Alcohol Swab
3. Sterile Cotton Ball or Gauze
4. Puncture-Resistant Sharps Container

Step 2 – Choose and Prepare Your Injection Site

2A – Choose your injection site
The recommended injection sites are the sides of the thighs and the arms.

Caution: Do not inject where your skin is scarred, bruised, tender, red or near any open wound.

2B – Clean the injection site with an alcohol swab

Do nottouch injection site area after cleaning.

2C – Remove the Red Cap
Hold the body of the Auto-injector in one hand and pull the Red Cap straight off.

Warning: Do notput or press thumb, fingers or hand over the Yellow Needle Guard, doing so may result in a needle stick injury

Step 3 – Inject the Medicine

3A – Place Auto-injector straight on your injection site
Place the Auto-injector straight on your injection site (90 degrees) with the Yellow Needle Guard end gently pressed against your skin.

3B – Perform Injection
Press and hold the Auto-injector down against your skin. You will hear the first "Click 1" as the injection starts. Continue to hold the device down until you hear the second "Click 2."
Wait 5 seconds before you remove the Auto-injector!
After "Click 2," continue to hold down and slowly count to 5 to make sure you receive your full dose.

Important: To receive your full dose, always hold the Auto-injector down on your injection site for additional time after you hear the second click. This allows all of the medicine to be delivered.

3C – Remove Auto-injector from skin
Remove the Auto-injector by lifting it straight away from your skin. The Yellow Needle Guard will drop down and lock over the needle.

Step 4 – Confirm Injection and Dispose the Auto-injector

4A – Confirm Red Color in Medicine Viewing Window
Look to confirm that the Red Plunger Rod has filled the Medicine Viewing Window. This means you received the full dose.

Caution: Call your healthcare provider if the Red Plunger Rod has not filled the Medicine Viewing Window. This may mean that only a partial dose was delivered.

Do nottry to reuse the Auto-injector.

4B – Disposal of the Auto-injector
Put your used Auto-injector, caps, needles, and sharps in an FDA-cleared sharps disposal container right away after use. Do not throw away (dispose of) loose needles and syringes in your household trash. Do not recycle your used sharps disposal container.
If you do not have a FDA-cleared sharps disposal container, you may use a household container that is: made of a heavy-duty plastic; can be closed with a tight-fitting, puncture-resistant lid, without sharps being able to come out; upright and stable during use; leak-resistant; and properly labeled to warn of hazardous waste inside the container.
When your sharps disposal container is almost full, you will need to follow your community guidelines for the right way to dispose of your sharps disposal container. There may be state or local laws about how you should throw away used needles and syringes. For more information about safe sharps disposal, and for specific information about sharps disposal in the state that you live in, go to the FDA's website at: http://www.fda.gov/safesharpsdisposal.
Do not dispose of your used sharps disposal container in your household trash unless your community guidelines permit this. Do not recycle your used sharps disposal container.
If needed, make sure you get a refill of your Auto-injector.

4C – Treat Injection Site

Treat the injection site with a cotton ball, gauze pad or bandage, as needed.

Do notrub the injection site.

Manufactured for
UPSHER-SMITH LABORATORIES, LLC
Maple Grove, MN 55369

ZEMBRACE and SymTouch are registered trademarks of Upsher-Smith Laboratories, LLC.

This product may be covered by one or more U.S. patent(s). See www.uslpatents.com.

This Instructions for Use has been approved by the U.S. Food and Drug Administration.

Revised: 2/2021

PRINCIPAL DISPLAY PANEL - 3 mg Syringe Carton

NDC 0245-0809-38

Rx only

Zembrace®SYMTOUCH®
(sumatriptan injection)

3 mg

For subcutaneous use only.

Each auto-injector contains a prefilled syringe with 0.5 mL of
sterile solution delivering 4.2 mg of sumatriptan succinate
equivalent to 3 mg of sumatriptan base, 4.15 mg sodium
chloride and water for injection.

See package insert for dosage information.

Store at 20° to 25°C (68° to 77°F).
Protect from light.

Manufactured for
UPSHER-SMITH LABORATORIES, LLC
Maple Grove, MN 55369

ZEMBRACE and SymTouch are registered trademarks of Upsher-Smith
Laboratories, LLC.

© 2019 Upsher-Smith Laboratories, LLC

UPSHER-SMITH